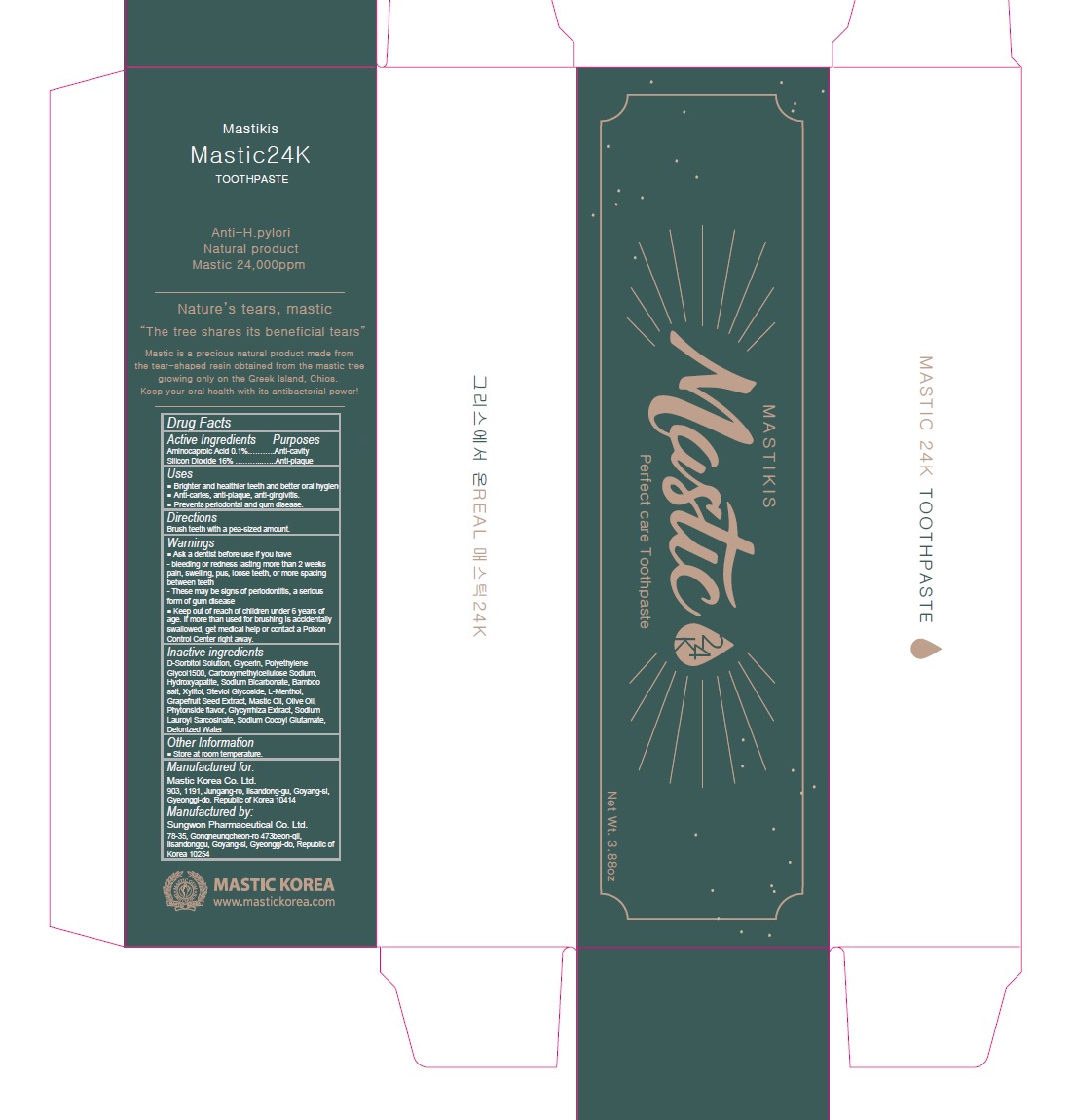 DRUG LABEL: Mastikis Mastic 24K
NDC: 79814-003 | Form: PASTE, DENTIFRICE
Manufacturer: Mastic Korea.Co.Ltd
Category: otc | Type: HUMAN OTC DRUG LABEL
Date: 20200814

ACTIVE INGREDIENTS: SILICON DIOXIDE 16 g/100 g; AMINOCAPROIC ACID 0.1 g/100 g
INACTIVE INGREDIENTS: SORBITOL; GLYCERIN; POLYETHYLENE GLYCOL 1600; CARBOXYMETHYLCELLULOSE SODIUM, UNSPECIFIED; TRIBASIC CALCIUM PHOSPHATE; SODIUM BICARBONATE; XYLITOL; STEVIOSIDE; LEVOMENTHOL; CITRUS PARADISI SEED; OLIVE OIL; LICORICE; SODIUM LAUROYL SARCOSINATE; SODIUM COCOYL GLUTAMATE; WATER

79814-003_Mastikis Mastic 24K toothpaste

ACTIVE INGREDIENT

Aminocaproic Acid 0.1%
Silica 16%

INACTIVE INGREDIENT

D-Sorbitol Solution, Glycerin, Polyethylene Glycol1500, Carboxymethylcellulose Sodium, Hydroxyapatite, Sodium Bicarbonate, Bamboo salt, Xylitol, Steviol Glycoside, L-Menthol, Grapefruit Seed Extract, Mastic Oil, Olive Oil, Phytonside flavour, Glycyrrhiza Extract, Sodium Lauroyl Sarcosinate, Sodium Cocoyl Glutamate, Deionized Water

Keep out of Reach of Children.

PURPOSE

Anti-cavity

Anti-plaque

WARNINGS

Ask a dentist before use if you have

- bleeding or redness lasting more than 2 weeks pain, swelling, pus, losse teeth, or more spacing between teeth

- These may be signs of periodontitis, a serious form of gum disease

INDICATIONS AND USAGE

- Brighter and healthier teeth and better oral hygiene

- Anti-caries, anti-plaque, anti--gingivitis

- Prevents periodontal and gum disease

DOSAGE AND ADMINISTRATION

Brush teeth with a pea-sized amount